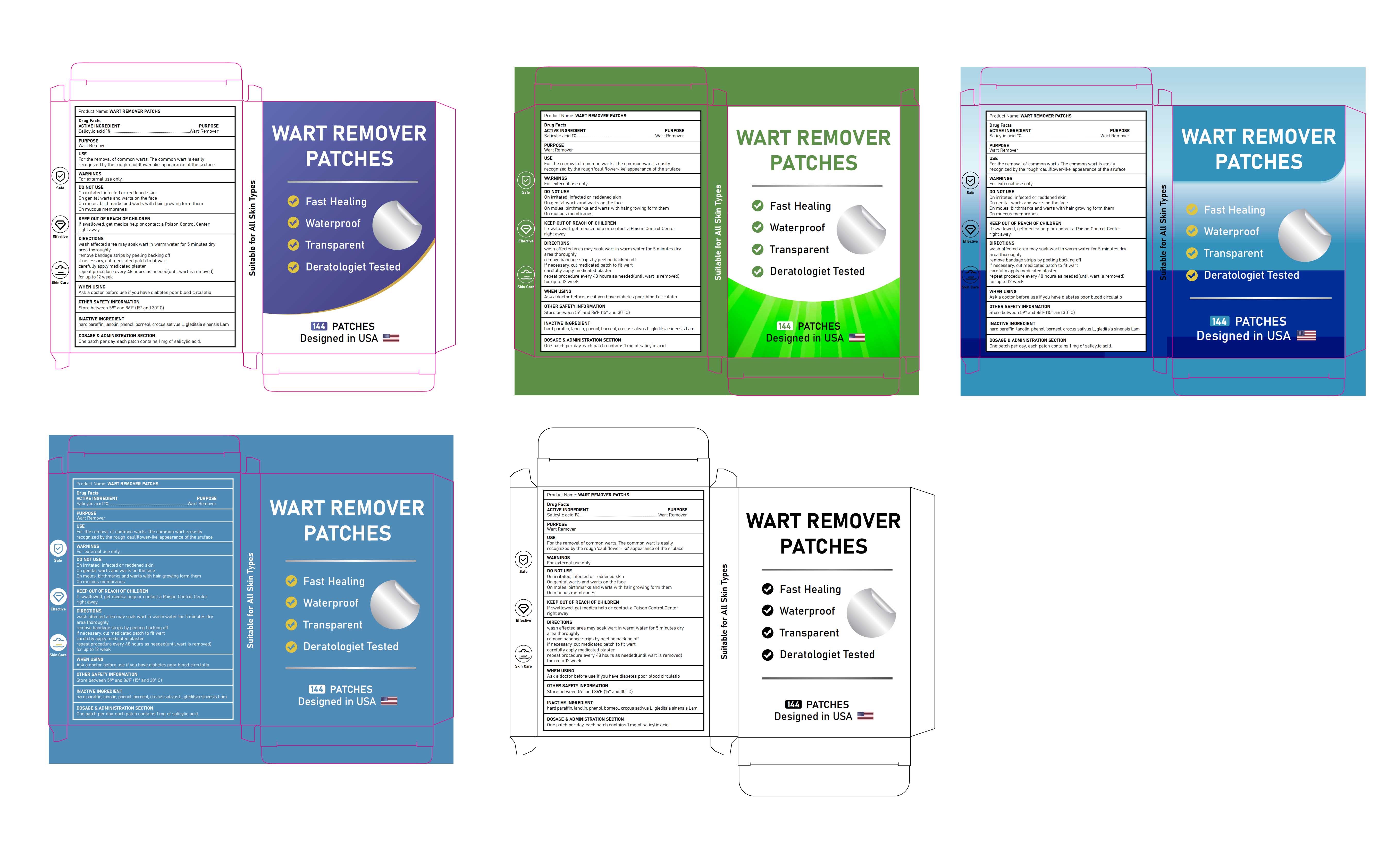 DRUG LABEL: WART REMOVER PATCHES
NDC: 85839-001 | Form: PATCH
Manufacturer: Shenzhen Finona Information Technology Co., Ltd
Category: otc | Type: HUMAN OTC DRUG LABEL
Date: 20250625

ACTIVE INGREDIENTS: SALICYLIC ACID 0.03 g/1 1
INACTIVE INGREDIENTS: PARAFFIN; PHENOL; BORNEOL; CROCUS SATIVUS WHOLE; LANOLIN; GLEDITSIA SINENSIS WHOLE

85839-001 WART REMOVER PATCHES

ACTIVE INGREDIENT

Salicylic acid 1%

PURPOSE

Wart Remover

INDICATIONS AND USAGE

For the removal of common warts. The common wart is easily recognized by the rough 'cauliflower-ike' appearance of the sruface

WARNINGS

For external use only.

DO NOT USE

On irritated, infected or reddened skin

On genital warts and warts on the face

On moles, birthmarks and warts with hair growing form them

On mucous membranes

Ask a doctor before use if you have diabetes poor blood circulatio

KEEP OUT OF REACH OF CHILDREN

If swallowed, get medica help or contact a Poison Control Center right away

DOSAGE AND ADMINISTRATION

One patch per day, each patch contains 1 mg of salicylic acid

INACTIVE INGREDIENT

hard paraffin
lanolin
phenol
borneol
crocus sativus L
gleditsia sinensis Lam